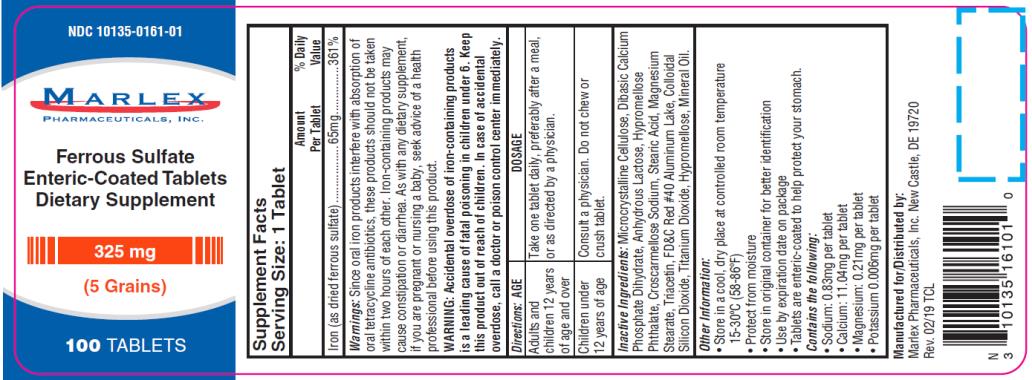 DRUG LABEL: Ferrous Sulfate
NDC: 10135-161 | Form: TABLET, COATED
Manufacturer: Marlex Pharmaceuticals Inc
Category: other | Type: DIETARY SUPPLEMENT
Date: 20190215

ACTIVE INGREDIENTS: FERROUS SULFATE 325 mg/1 1
INACTIVE INGREDIENTS: MICROCRYSTALLINE CELLULOSE; DIBASIC CALCIUM PHOSPHATE DIHYDRATE; ANHYDROUS LACTOSE; CROSCARMELLOSE SODIUM; STEARIC ACID; MAGNESIUM STEARATE; TRIACETIN; FD&C RED NO. 40; SILICON DIOXIDE; TITANIUM DIOXIDE; HYPROMELLOSE, UNSPECIFIED; MINERAL OIL

Ferrous Sulfate

Supplement Facts

Serving Size: 1 Tablet

Amount %Daily
Per Tablet Value

Iron (as dried ferrous sulfate)…………….…65mg…………………….361%

Ferrous Sulfate Enteric-Coated Tablets Iron Supplement

Warnings

Since oral iron products interfere with absorption of oral tetracycline antibiotics, these products should not be taken within two hours of each other. Iron-containing products may cause constipation or diarrhea. As with any dietary supplement, if you are pregnant or nursing a baby, seek advice of a health professional before using this product.

WARNING: Accidental overdose of iron-containing products is a leading cause of fatal poisoning in children under 6. Keep this product out of reach of children. In case of accidental overdose, call a doctor or poison control center immediately.

Directions

Adults and children 12 years of age and over: Take one tablet daily, preferably after a meal, or as directed by a physician.

Children under 12 years of age: Consult a physician. Do not chew or crush tablet.

Inactive Ingredients:

Microcrystalline Cellulose, Dibasic Calcium Phosphate Dihydrate, Anhydrous Lactose, Hypromellose Phthalate, Croscarmellose Sodium, Stearic Acid, Magnesium Stearate, Triacetin, FD&C Red #40 Aluminum Lake, Colloidal Silicon Dioxide, Titanium Dioxide, Hypromellose, Mineral Oil.

Other Information:

• Store in a cool, dry place at controlled room temperature

15-30ºC (58-86ºF)

• Protect from moisture

• Store in original container for better identification

• Use by expiration date on package

• Tablets are enteric-coated to help protect your stomach.

Contains the following:

• Sodium: 0.83mg per tablet

• Calcium: 11.04mg per tablet

• Magnesium: 0.21mg per tablet

• Potassium 0.006mg per tablet

Manufactured for & Distributed by:

Marlex Pharmaceuticals, Inc.

New Castle, DE 19720

Rev: 02/19TCL

PRINCIPAL DISPLAY PANEL

NDC 10135-0161-01
Ferrous Sulfate
Enteric-Coated Tablets
Dietary Supplement
325 mg
100 TABLETS